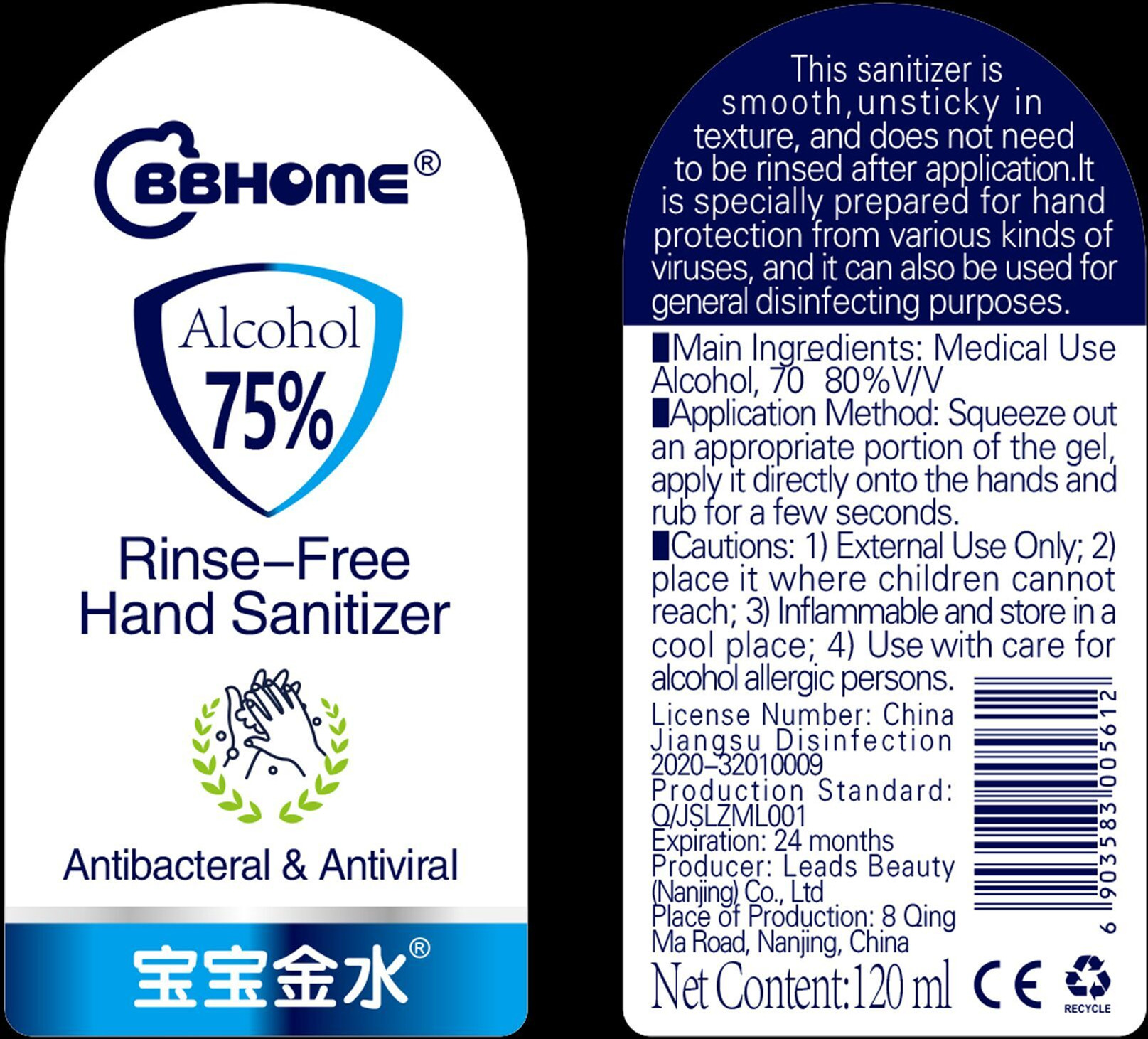 DRUG LABEL: BBHOME Rinse-Free Hand Sanitizer
NDC: 52809-001 | Form: GEL
Manufacturer: Leads Beauty (Nanjing) Co., Ltd.
Category: otc | Type: HUMAN OTC DRUG LABEL
Date: 20200423

ACTIVE INGREDIENTS: ALCOHOL 85.5 mL/120 mL
INACTIVE INGREDIENTS: LONICERA JAPONICA FLOWER; WATER; ETHYLHEXYLGLYCERIN; PHENOXYETHANOL; TROLAMINE; GLYCERIN; DENDRANTHEMA INDICUM FLOWER; 2,2-DINITROPROPYL ACRYLATE

DOSAGE AND ADMINISTRATION

Inflammable and store in a cool place;

INACTIVE INGREDIENT

Water

Ethylhexylglycerol

Triethanolamine

glycerin

Phenoxyethanol

Acrylic

LONICERA JAPONICA

CHRYSANTHEMUM INDICUM

INDICATIONS AND USAGE

Squeeze out an appropriate portion of the gel,apply it directly onto the hands and rub for a few seconds.

ACTIVE INGREDIENT

Ethanol

keep out of children

PURPOSE

Disinfection
Sterilization

WARNINGS

1.External Use Only;

2.place it where children cannot reach;

3. Inflammable and store ina cool place;

4. Use with care for alcohol allergic persons.